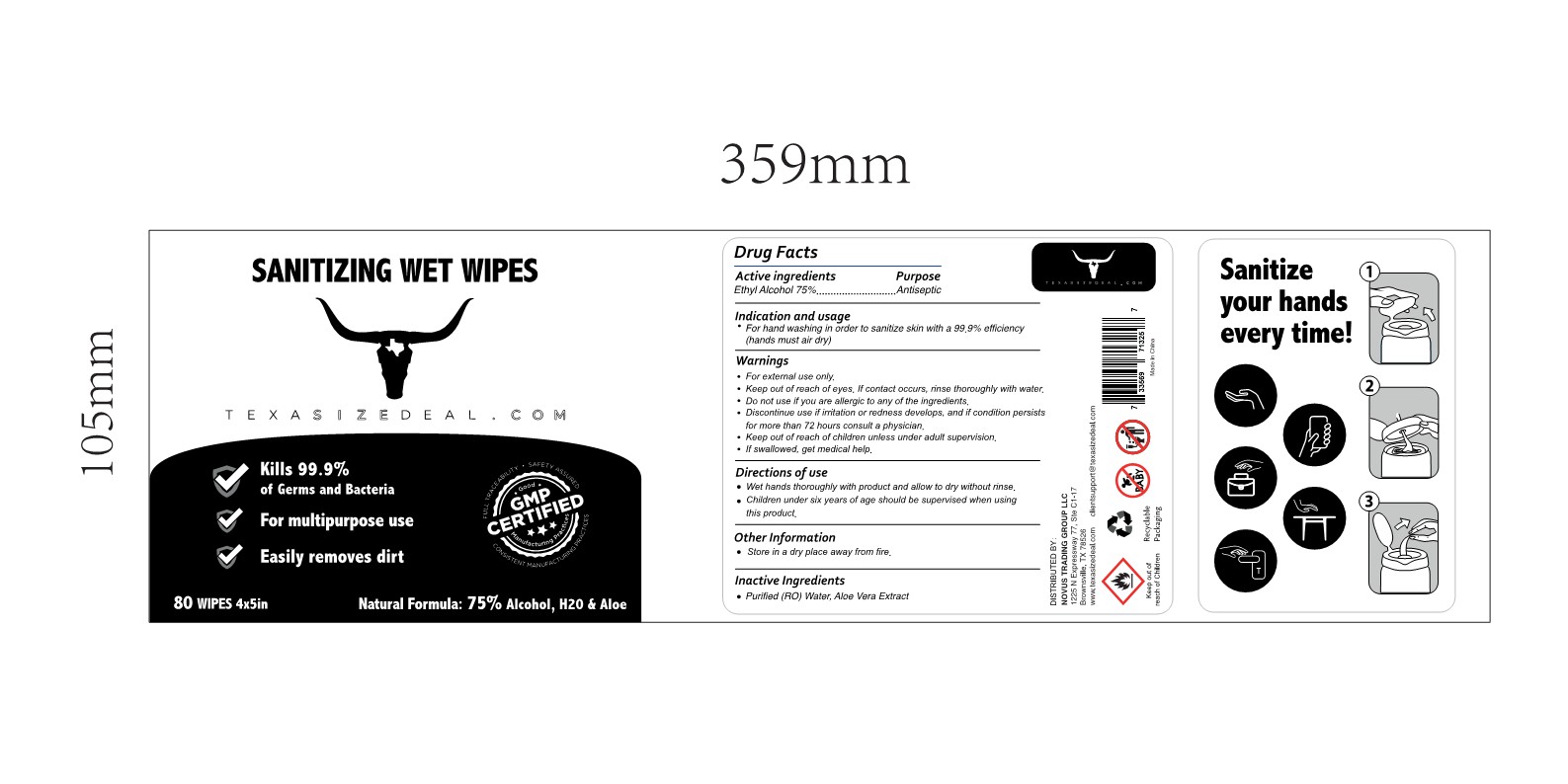 DRUG LABEL: HAND SANITIZER
NDC: 80402-001 | Form: CLOTH
Manufacturer: NOVUS TRADING GROUP LLC
Category: otc | Type: HUMAN OTC DRUG LABEL
Date: 20200901

ACTIVE INGREDIENTS: ALCOHOL 75 mL/75 mL
INACTIVE INGREDIENTS: WATER; ALOE VERA LEAF

This is a hand sanitizer manufactured according to the Temporary Policy for Preparation of Certain Alcohol-Based Hand Sanitizer Products During the Public Health Emergency (CoViD-19); Guidance for Industry.

The hand sanitizer is manufactured using only the following United States Pharmacopoeia (USP) grade ingredients in the preparation of the product (percentage in final product formulation) consistent with World Health Organization (WHO) recommendations:

1. Alcohol (ethanol) (USP or Food Chemical Codex (FCC) grade) (75%, volume/volume (v/v)) in an aqueous solution denatured according to Alcohol and Tobacco Tax and Trade Bureau regulations in 27 CFR part 20.
2. Sterile distilled water or boiled cold water.
3. Aloe Vera

The firm does not add other active or inactive ingredients. Different or additional ingredients may impact the quality and potency of the product.

Active Ingredient

Ethyl Alcohol 75% v/v. Purpose: Antiseptic

Purpose

Antiseptic

Indications and usage

For hand washing in order to sanitize skin with 99.9% efficiency (hands must air dry)

Warnings

For external use only.

Keep out of reach of eyes. If contact occurs, rinse thoroughly with water.

Do not use if you are allergic to any of the ingredients.

Discontinue use if irritation or redness develops, and if condition persist for more than 72 hours consult a physician.

Keep out of reach of children unless under adult supervision.

If swallowed, get medical help.

Warnings

Keep out of reach of children unless under adult supervision.

Directions of use

- Wet hands thoroughly with product and allow to dry without rinse.
- Children undersiz years of age should be supervised when using this product.

Other Information

Store in a dry place away from fire.

Inactive ingredients

Purified (RO) Water, Aloe Vera

Package Label - Principal Display Panel

80 SANITIZING WET WIPES with 75% Ethyl Alcohol, NDC: 80402-001-80